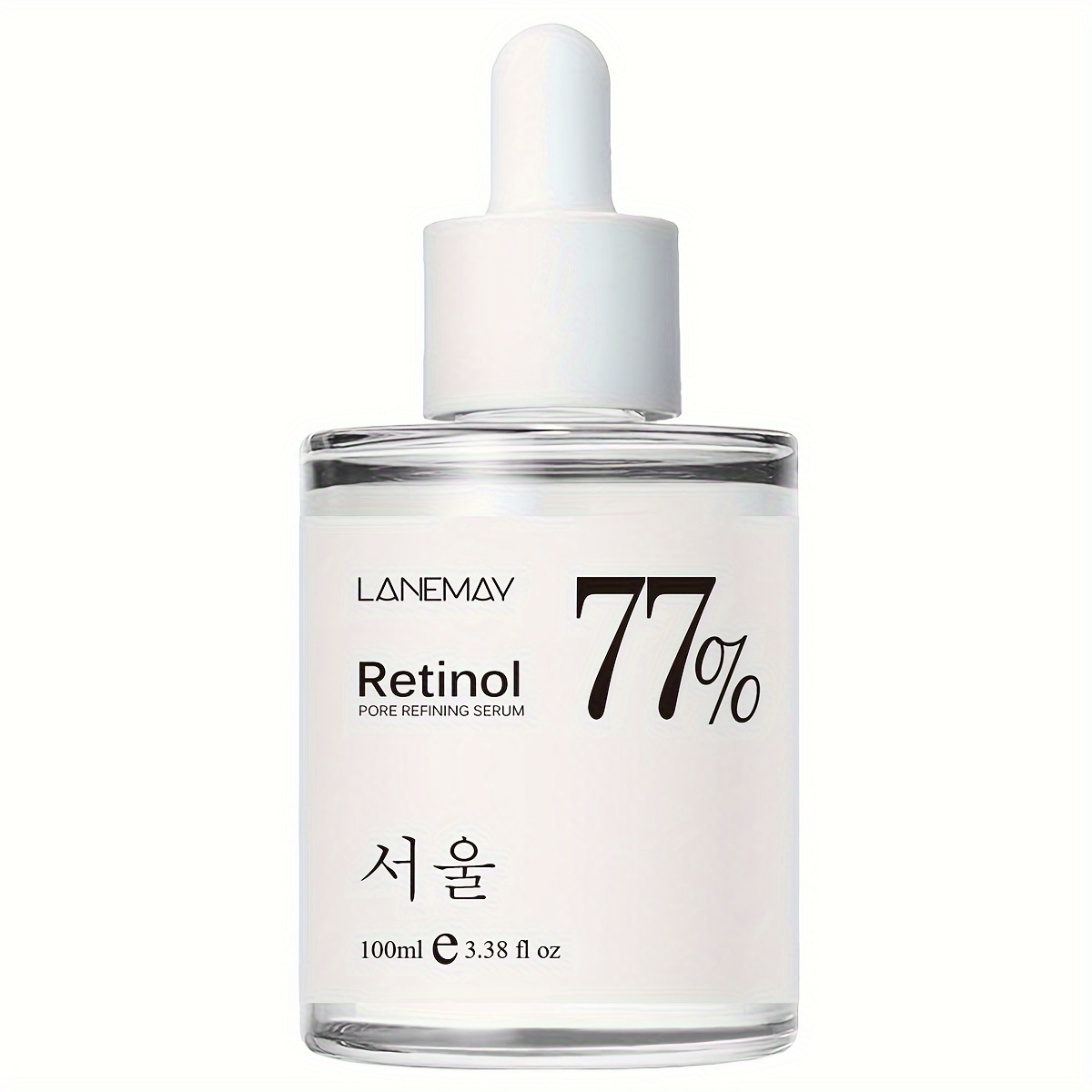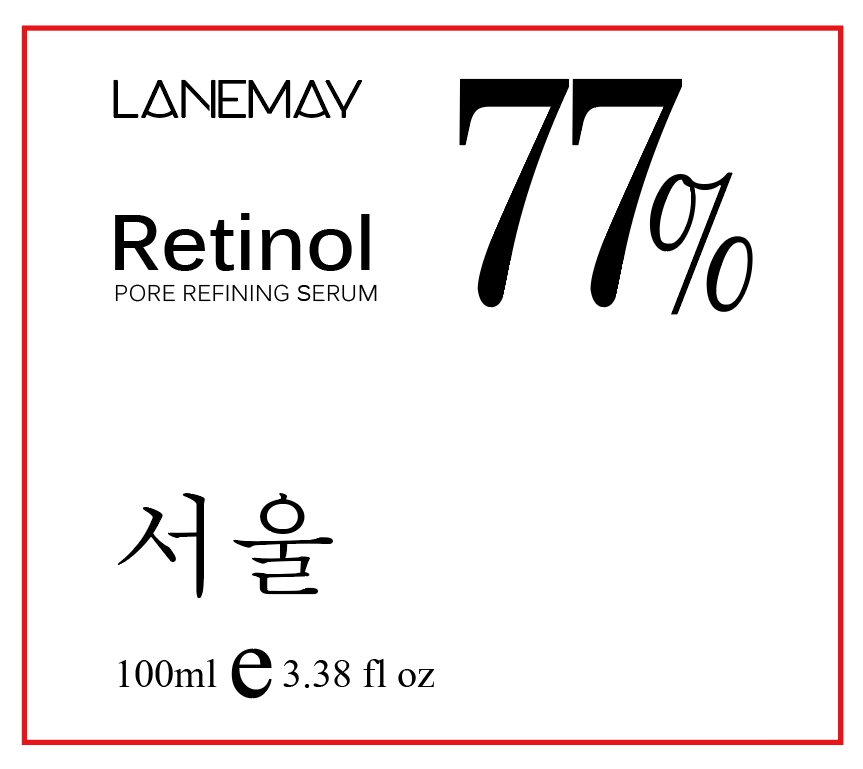 DRUG LABEL: RETINOL PORE REFINING SERUM
NDC: 84025-026 | Form: LIQUID
Manufacturer: Guangzhou Yanxi Biotechnology Co., Ltd
Category: otc | Type: HUMAN OTC DRUG LABEL
Date: 20240331

ACTIVE INGREDIENTS: BIOTINOYL TRIPEPTIDE-1 10 mg/100 mL
INACTIVE INGREDIENTS: WATER

DOSAGE AND ADMINISTRATION

use as a normal facial serum

WARNINGS

Keep out of Children

INACTIVE INGREDIENT

aqua

INDICATIONS AND USAGE

Apply to affected area twice per day on cleansed skin.

Keep out of reach of children.

PURPOSE

Deep hydration, moisturizing the skin